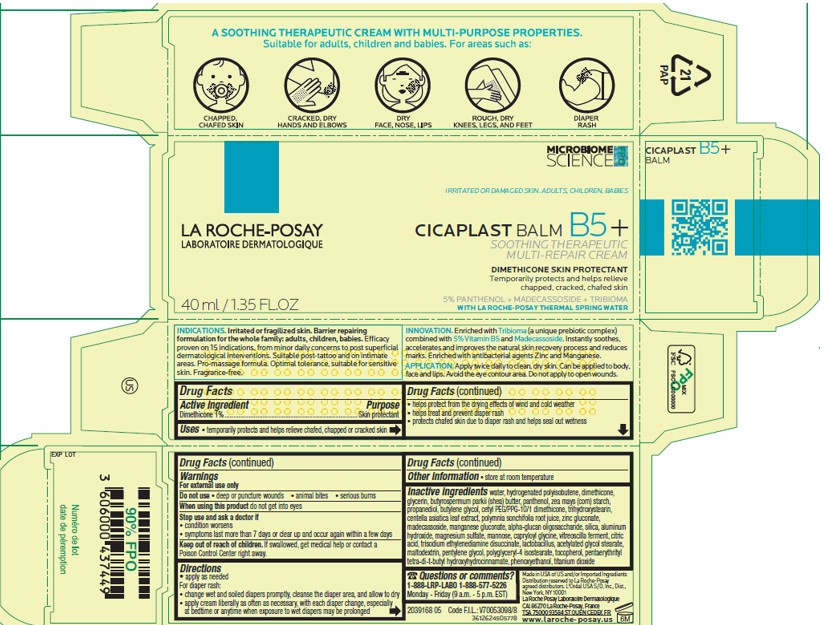 DRUG LABEL: La Roche Posay Laboratoire Dermatologique Cicaplast Balm B5 Therapeutic Multipurpose
NDC: 69625-743 | Form: CREAM
Manufacturer: Cosmetique Active Production
Category: otc | Type: HUMAN OTC DRUG LABEL
Date: 20250724

ACTIVE INGREDIENTS: DIMETHICONE 10 mg/1 mL
INACTIVE INGREDIENTS: WATER; HYDROGENATED POLYBUTENE (1300 MW); GLYCERIN; SHEA BUTTER; PANTHENOL; BUTYLENE GLYCOL; PROPANEDIOL; CETYL PEG/PPG-10/1 DIMETHICONE (HLB 2); TRIHYDROXYSTEARIN; ZINC GLUCONATE; MADECASSOSIDE; MANGANESE GLUCONATE; SILICON DIOXIDE; ALUMINUM HYDROXIDE; ZEA MAYS (CORN) STARCH; CENTELLA ASIATICA WHOLE; POLYMNIA SONCHIFOLIA ROOT JUICE; ALPHA-GLUCAN OLIGOSACCHARIDE; MANNOSE; CAPRYLOYL GLYCINE; TRISODIUM ETHYLENEDIAMINE DISUCCINATE; LACTOBACILLUS; MALTODEXTRIN; PENTYLENE GLYCOL; MAGNESIUM SULFATE, UNSPECIFIED FORM; CITRIC ACID MONOHYDRATE; ACETYLATED GLYCOL STEARATE; POLYGLYCERYL-4 ISOSTEARATE; TOCOPHEROL; PENTAERYTHRITOL TETRAKIS(3-(3,5-DI-TERT-BUTYL-4-HYDROXYPHENYL)PROPIONATE); PHENOXYETHANOL; TITANIUM DIOXIDE

Drug Facts

Active ingredient

Dimethicone 1%

Purpose

Skin protectant

Uses

- temporarily protects and helps relieve chafed, chapped or cracked skin
- helps protect from the drying effects of wind and cold weather
- helps treat and prevent diaper rash
- protects chafed skin due to diaper rash and helps seal out wetness

Warnings

For external use only

Do not use

- on deep or puncture wounds
- animal bites
- serious burns

When using this product

do not get into eyes

Stop use and ask a doctor if

- condition worsens
- symptoms last more than 7 days or clear up and occur again within a few days

Keep out of reach of children.

If swallowed, get medical help or contact a Poison Control Center right away.

Directions

- apply as needed

For diaper rash:

- change wet and soiled diapers promptly, cleanse the diaper area, and allow to dry
- apply cream liberally as often as necessary, with each diaper change, especially at bedtime or anytime when exposure to wet diapers may be prolonged

Other information

● store at room temperature

Inactive ingredients

wwater, hydrogenated polyisobutene, dimethicone, glycerin, butyrospermum parkii (shea) butter, panthenol, zea mays (corn) starch, propanediol, butylene glycol, cetyl PEG/PPG-10/1 dimethicone, trihydroxystearin, centella asiatica leaf extract, polymnia sonchifolia root juice, zinc gluconate, madecassoside, manganese gluconate, alpha-glucan oligosaccharide, silica, aluminum hydroxide, magnesium sulfate, mannose, capryloyl glycine, vitreoscilla ferment, citric acid, trisodium ethylenediamine disuccinate, lactobacillus, acetylated glycol stearate, maltodextrin, pentylene glycol, polyglyceryl-4 isostearate, tocopherol, pentaerythrityl tetra-di-t-butyl hydroxyhydrocinnamate, phenoxyethanol, titanium dioxide

Questions or comments?

1-888-LRP-LABO 1-888-577-5226

Monday - Friday (9 a.m. - 5 p.m. EST)